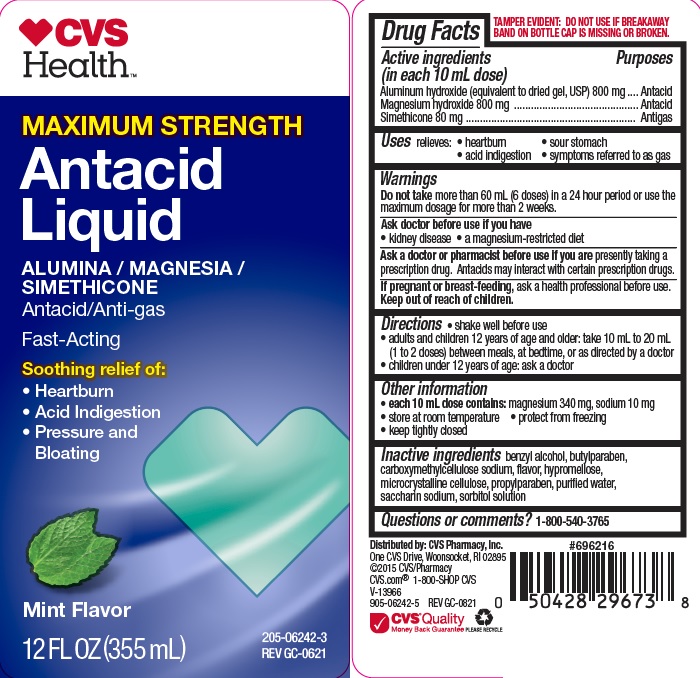 DRUG LABEL: MAXIMUM STRENGTH ANTACID MINT
NDC: 69842-296 | Form: LIQUID
Manufacturer: CVS
Category: otc | Type: HUMAN OTC DRUG LABEL
Date: 20251111

ACTIVE INGREDIENTS: ALUMINUM HYDROXIDE 800 mg/10 mL; MAGNESIUM HYDROXIDE 800 mg/10 mL; DIMETHICONE 80 mg/10 mL
INACTIVE INGREDIENTS: HYPROMELLOSES; CELLULOSE, MICROCRYSTALLINE; BUTYLPARABEN; PROPYLPARABEN; WATER; SACCHARIN SODIUM; SORBITOL SOLUTION; BENZYL ALCOHOL; CARBOXYMETHYLCELLULOSE SODIUM

CVS ANTACID MINT MAX

Active ingredients (in each 10 mL dose)

Aluminum hydroxide 800 mg (equivalent to dried gel, USP)
Magnesium hydroxide 800 mg
Simethicone 80 mg

Purposes

Antacid

Antigas

Uses

relieves

- heartburn
- sour stomach
- acid indigestion
- the symptoms referred to as gas

Warnings

Do not take more than 60 mL (6 doses) in a 24 hour period or use the
maximum dosage for more than 2 weeks.

Ask a doctor before use if you have

• kidney disease
• a magnesium-restricted diet

Ask a doctor or pharmacist before use if you are presently taking a

prescription drug. Antacids may interact with certain prescription drugs.

If pregnant or breast-feeding, ask a health professional before use.

Keep out of reach of children.

Directions

- shake well before use
- adults and children 12 years of age and older:take 10 mL to 20 mL (1 to 2 doses) between meals, at bedtime, or as directed by a doctor
- children under under 12 years of age: ask a doctor

Other information

- each 10 mL dose contains: magnesium 340 mg, sodium 10 mg
- protect from freezing
- store at room temperature
- keep tightly closed

Inactive ingredients

benzyl alcohol, butylparaben, carboxymethylcellulose sodium, flavor, hypromellose, microcrystalline cellulose, propylparaben, purified water, saccharin sodium, sorbitol solution

Questions or comments?

1-800-540-3765